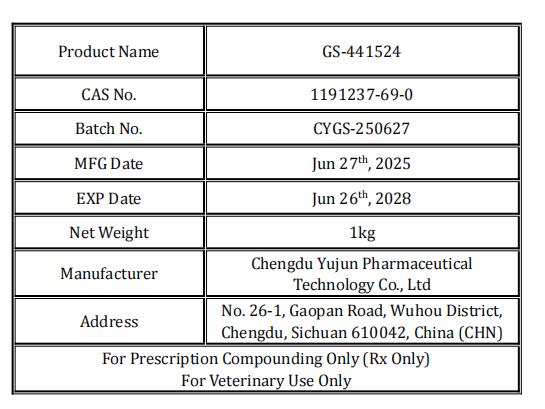 DRUG LABEL: GS-441524
NDC: 86230-126 | Form: POWDER
Manufacturer: Chengdu Yujun Pharmaceutical Technology Co., Ltd
Category: other | Type: BULK INGREDIENT - ANIMAL DRUG
Date: 20250820

ACTIVE INGREDIENTS: GS-441524 1 kg/1 kg

GS-441524

GS-441524

Add image transcription here...